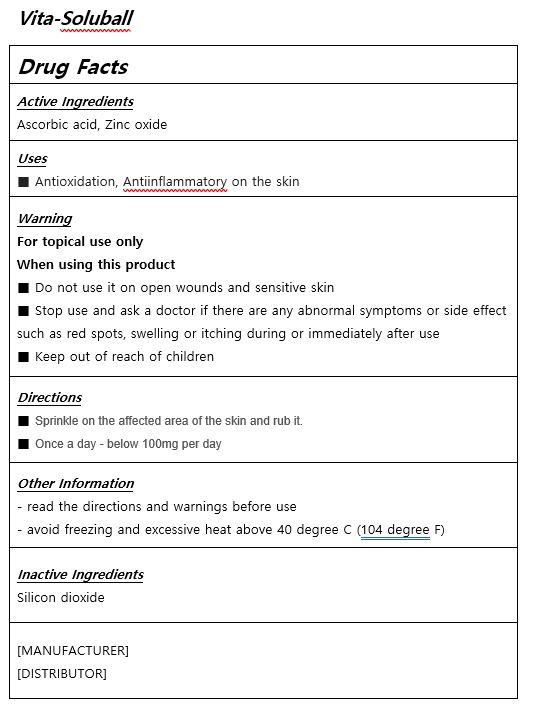 DRUG LABEL: Vita Soluball
NDC: 84020-0001 | Form: POWDER
Manufacturer: Silexn Technology Co.,Ltd.
Category: otc | Type: HUMAN OTC DRUG LABEL
Date: 20240123

ACTIVE INGREDIENTS: ZINC OXIDE 40 mg/1000 mg; ASCORBIC ACID 200 mg/1000 mg
INACTIVE INGREDIENTS: BUTYLENE GLYCOL

Drug Facts

ACTIVE INGREDIENT

Ascorbic acid 200mg, Zinc oxide 40mg per 1000mg

INACTIVE INGREDIENT

silicon dioxide

PURPOSE

Antioxidation, Antiinflammatory on the skin

KEEP OUT OF REACH OF THE CHILDREN

INDICATIONS AND USAGE

Sprinkle on the affected area of the skin and rub it.

Once a day - below 100mg per day

WARNINGS

Stop using it immediately if there are signs of skin rashes or hypersensitivity.

DOSAGE AND ADMINISTRATION

for topical use only